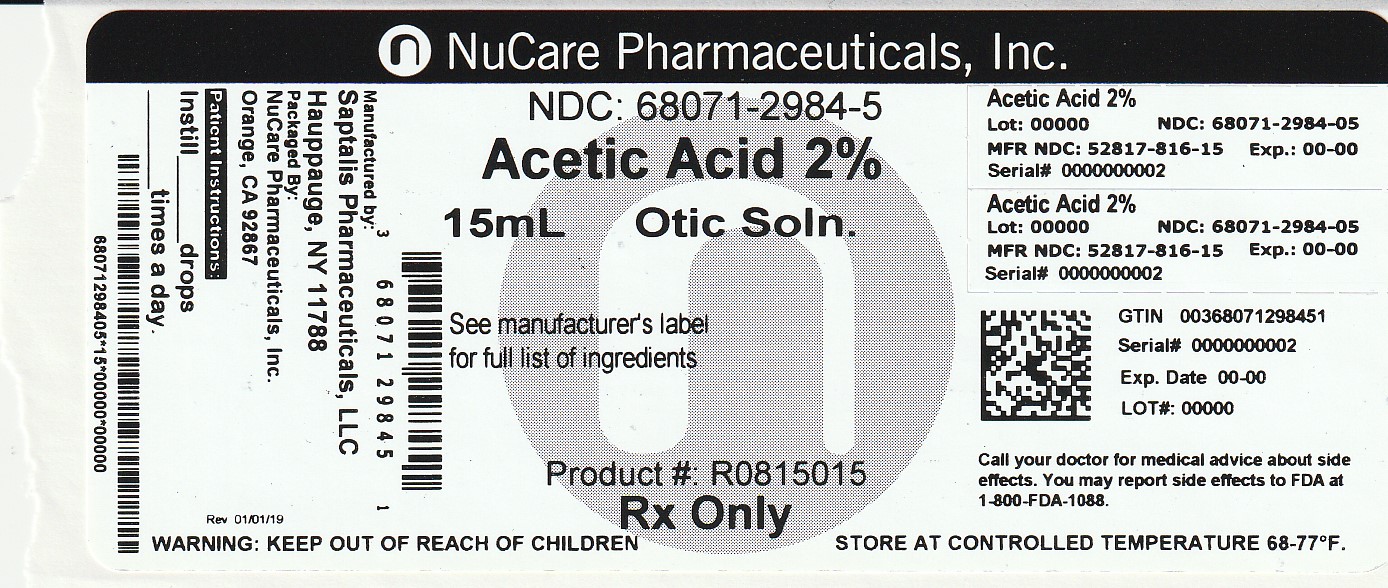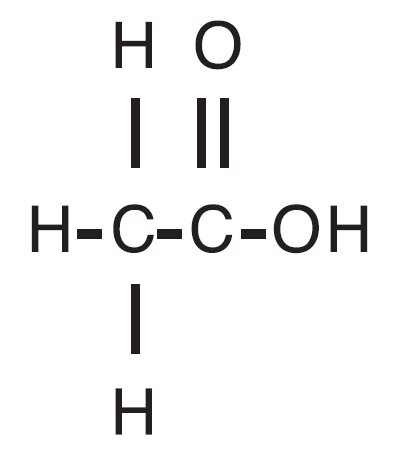 DRUG LABEL: Acetic Acid
NDC: 68071-2984 | Form: SOLUTION
Manufacturer: NuCare Pharmaceuticals,Inc.
Category: prescription | Type: HUMAN PRESCRIPTION DRUG LABEL
Date: 20250210

ACTIVE INGREDIENTS: ACETIC ACID 20.65 mg/1 mL
INACTIVE INGREDIENTS: PROPYLENE GLYCOL; BENZETHONIUM CHLORIDE; PROPYLENE GLYCOL DIACETATE; SODIUM ACETATE; ANHYDROUS CITRIC ACID

Acetic Acid Otic Solution, USP

DESCRIPTION

Acetic acid otic solution, USP is a solution of acetic acid (2%), in a propylene glycol vehicle containing propylene glycol diacetate (3%), benzethonium chloride (0.02%), sodium acetate (0.015%), and citric acid. The molecular formula for acetic acid is CH3COOH, with a molecular weight of 60.05. The structural formula is:

Acetic acid otic solution, USP is available as a nonaqueous otic solution buffered at pH 3 for use in the external ear canal.

CLINICAL PHARMACOLOGY

Acetic acid is antibacterial and antifungal; propylene glycol is hydrophilic and provides a low surface tension; benzethonium chloride is a surface active agent that promotes contact of the solution with tissues.

INDICATIONS AND USAGE

For the treatment of superficial infections of the external auditory canal caused by organisms susceptible to the action of the antimicrobial.

CONTRAINDICATIONS

Hypersensitivity to acetic acid otic solution or any of the ingredients. Perforated tympanic membrane is considered a contraindication to the use of any medication in the external ear canal.

WARNINGS

Discontinue promptly if sensitization or irritation occurs.

PRECAUTIONS

Transient stinging or burning may be noted occasionally when the solution is first instilled into the acutely inflamed ear.

PEDIATRIC USE

Safety and effectiveness in pediatric patients below the age of 3 years have not been established.

ADVERSE REACTIONS

Stinging or burning may be noted occasionally; local irritation has occurred very rarely.

To report SUSPECTED ADVERSE REACTIONS, contact Saptalis Pharmaceuticals, LLC at 1-833-727-8254 or FDA at 1800-FDA-1088 or www.fda.gov/medwatch.

DOSAGE AND ADMINISTRATION

Carefully remove all cerumen and debris to allow acetic acid otic solution to contact infected surfaces directly. To promote continuous contact, insert a wick of cotton saturated with acetic acid otic solution into the ear canal; the wick may also be saturated after insertion. Instruct the patient to keep the wick in for at least 24 hours and to keep it moist by adding 3 drops to 5 drops of acetic acid otic solution every 4 hours to 6 hours. The wick may be removed after 24 hours but the patient should continue to instill 5 drops of acetic acid otic solution 3 times or 4 times daily thereafter, for as long as indicated. In pediatric patients, 3 drops to 4 drops may be sufficient due to the smaller capacity of the ear canal.

HOW SUPPLIED

Acetic acid otic solution, USP, containing 2% acetic acid, is available in 15 mL measured‑drop, safety-tip plastic bottles.

NDC 68071-2984-5 15 mL Bottle

STORAGE

Store at 20° to 25°C (68° to 77°F) [see USP Controlled Room Temperature]. Keep container tightly closed.

Manufactured by:

Saptalis Pharmaceuticals, LLC

Hauppauge, NY 11788

Distributed by:

TruPharma, LLC

Tampa, FL 33609

Rev. 03/20-R1